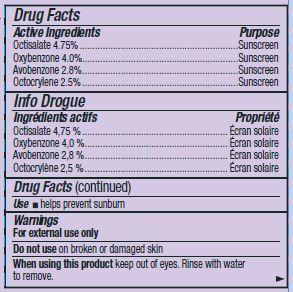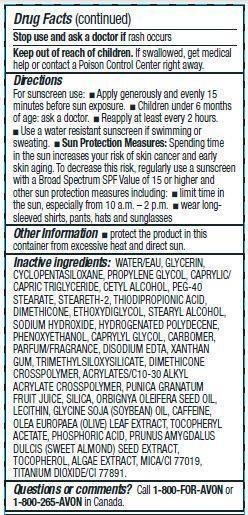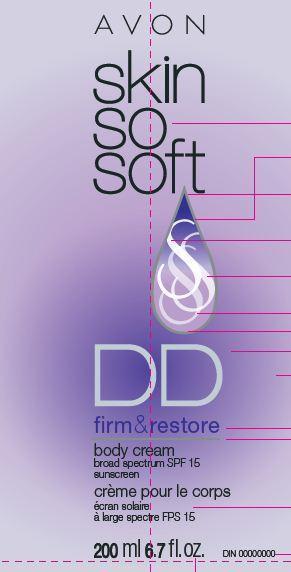 DRUG LABEL: Skin So Soft
NDC: 10096-0317 | Form: CREAM
Manufacturer: New Avon LLC
Category: otc | Type: HUMAN OTC DRUG LABEL
Date: 20190101

ACTIVE INGREDIENTS: OCTISALATE 47.5 mg/1 mL; OXYBENZONE 40 mg/1 mL; AVOBENZONE 28 mg/1 mL; OCTOCRYLENE 25 mg/1 mL
INACTIVE INGREDIENTS: WATER

Skin So Soft DD Body Cream

Active ingredient
Octisalate 4.75%.............................
Oxybenzone 4.0%...........................
Avobenzone 2.8%...........................
Octocrylene 2.5%.............................

Purpose
.................................Sunscreen

.................................Sunscreen

.................................Sunscreen

.................................Sunscreen

Uses
• helps prevent sunburn

Warnings

For external use only

Do not use on damaged or broken skin

When using this product keep out of eyes. Rinse with water to remove.

Stop use and ask a doctor if rash occurs

Keep out of reach of children. If swallowed, get medical help or contact a Poison Control Center right away.

Directions

For sunscreen use:
• apply liberally 15 minutes before sun exposure
• children under 6 months of age: ask a doctor
• reapply at least every 2 hours
• use a water resistant sunscreen if swimming or sweating

•Sun Protection Measures: Spending time in the sun increases your risk of skin cancer and early skin aging. To decrease this risk, regularly use a sunscreen with a Broad Spectrum SPF Value of 15 or higher and other sun protection measures including:

•limit time in the sun, especially from 10 a.m. – 2 p.m.

•wear longsleeved shirts, pants, hats and sunglasses

Other information

• protect the product in this container from excessive heat and direct sun

Inactive Ingredients:
WATER/EAU, GLYCERIN, CYCLOPENTASILOXANE, PROPYLENE GLYCOL, CAPRYLIC/CAPRIC TRIGLYCERIDE, CETYL ALCOHOL, PEG-40 STEARATE, STEARETH-2, THIODIPROPIONIC ACID, DIMETHICONE, ETHOXYDIGLYCOL, STEARYL ALCOHOL, SODIUM HYDROXIDE, HYDROGENATED POLYDECENE, PHENOXYETHANOL, CAPRYLYL GLYCOL, CARBOMER, PARFUM/FRAGRANCE, DISODIUM EDTA, XANTHAN GUM, TRIMETHYLSILOXYSILICATE, DIMETHICONE CROSSPOLYMER, ACRYLATES/C10-30 ALKYL ACRYLATE CROSSPOLYMER, PUNICA GRANATUM FRUIT JUICE, SILICA, ORBIGNYA OLEIFERA SEED OIL, LECITHIN, GLYCINE SOJA (SOYBEAN) OIL, CAFFEINE, OLEA EUROPAEA (OLIVE) LEAF EXTRACT, TOCOPHERYL ACETATE, PHOSPHORIC ACID, PRUNUS AMYGDALUS DULCIS (SWEET ALMOND) SEED EXTRACT, TOCOPHEROL, ALGAE EXTRACT, MICA/CI 77019, TITANIUM DIOXIDE/CI 77891.

Questions or Comments?
Call toll free 1-800-FOR-AVON or 1-800-265-AVON in Canada